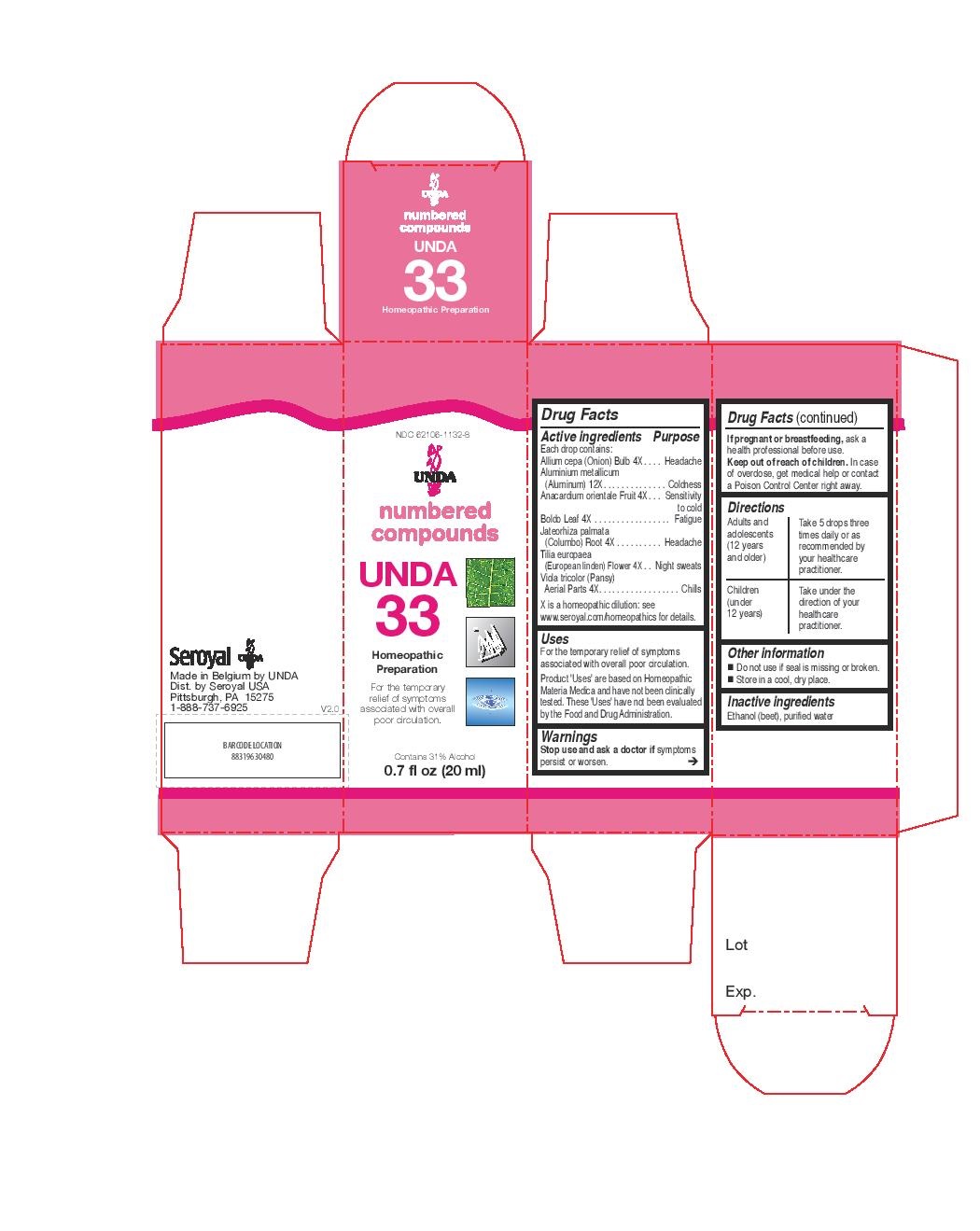 DRUG LABEL: Unda 33
NDC: 62106-1132 | Form: LIQUID
Manufacturer: Seroyal USA
Category: homeopathic | Type: HUMAN OTC DRUG LABEL
Date: 20221109

ACTIVE INGREDIENTS: ONION 4 [hp_X]/20 mL; TILIA X EUROPAEA FLOWER 4 [hp_X]/20 mL; JATEORHIZA CALUMBA ROOT 4 [hp_X]/20 mL; VIOLA TRICOLOR 4 [hp_X]/20 mL; PEUMUS BOLDUS LEAF 4 [hp_X]/20 mL; SEMECARPUS ANACARDIUM JUICE 4 [hp_X]/20 mL; ALUMINUM 12 [hp_X]/20 mL
INACTIVE INGREDIENTS: ALCOHOL; WATER

UNDA 33

Active ingredients

Each drop contains:
Allium cepa (Onion) Bulb 4X
Aluminium metallicum (Aluminum) 12X
Anacardium orientale Fruit 4X
Boldo Leaf 4X
Jateorhiza palmata (Columbo) Root 4X
Tilia europaea (European linden) Flower 4X
Viola tricolor (Pansy) Aerial Parts 4X

Uses
For the temporary relief of symptoms associated with overall poor circulation.

Warnings
If pregnant or breastfeeding, ask a health professional before use.

Keep out of reach of children.

In case of overdose, get medical help or contact a
Poison Control Center right away.

If symptoms persist or worsen, consult your healthcare practitioner.

PREGNANCY OR BREAST FEEDING

If pregnant or breastfeeding, ask a health professional before use.

Keep out of reach of children.

OVERDOSAGE

In case of overdose, get medical help or contact a

Poison Control Center right away.

Stop use and ask a doctor if symptoms persist or worsen.

Inactive Ingredients:

Ethanol (beet),
purified water

Other information
Do not use if seal is missing or broken.
Store in a cool, dry place.

Directions
Adults and adolescents (12 years and older)

Take 5 drops three times daily or as recommended by your healthcare practitioner.
Children (under 12 years)
Take under the direction of your healthcare practitioner.

Uses
For the temporary relief of symptoms associated with overall poor circulation.

Directions
Adults and adolescents (12 years and older)

Take 5 drops three times daily or as recommended by your healthcare practitioner.
Children (under 12 years)
Take under the direction of your healthcare practitioner.

PACKAGE LABEL

NDC 62106-1132-8

UNDA

numbered compounds

UNDA 33

Homeopathic Preparation

For the temporary relief of symptoms
associated with overall poor circulation.

Contains 31% Alcohol
0.7 fl oz (20 ml)